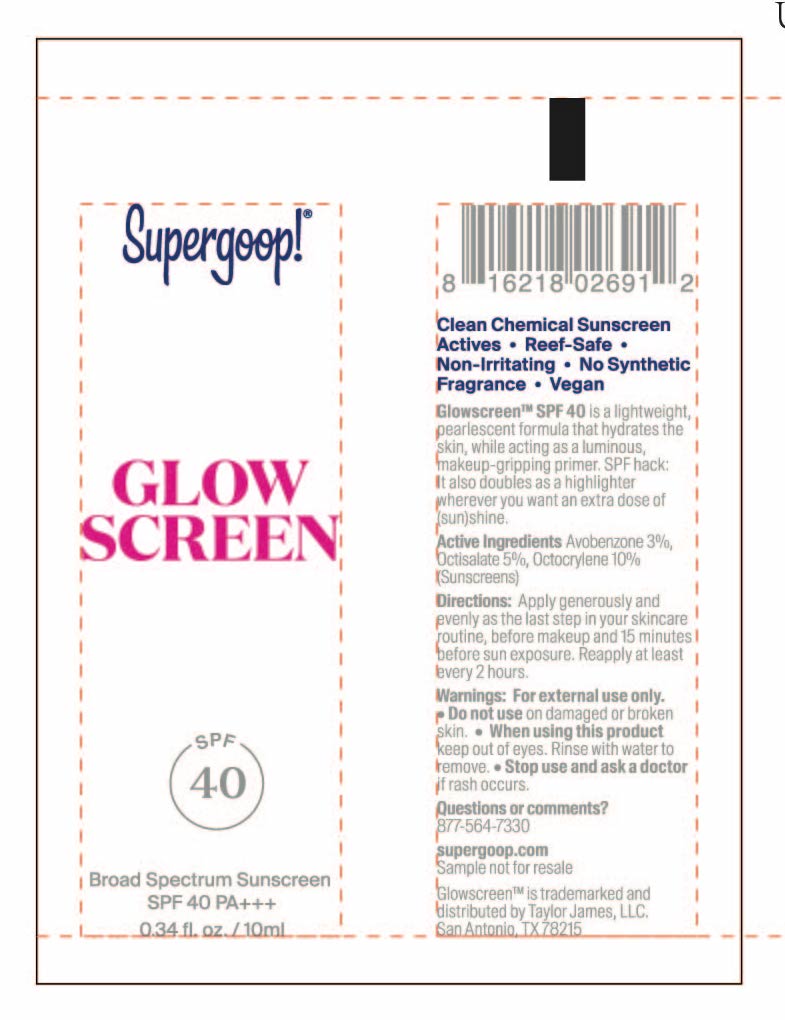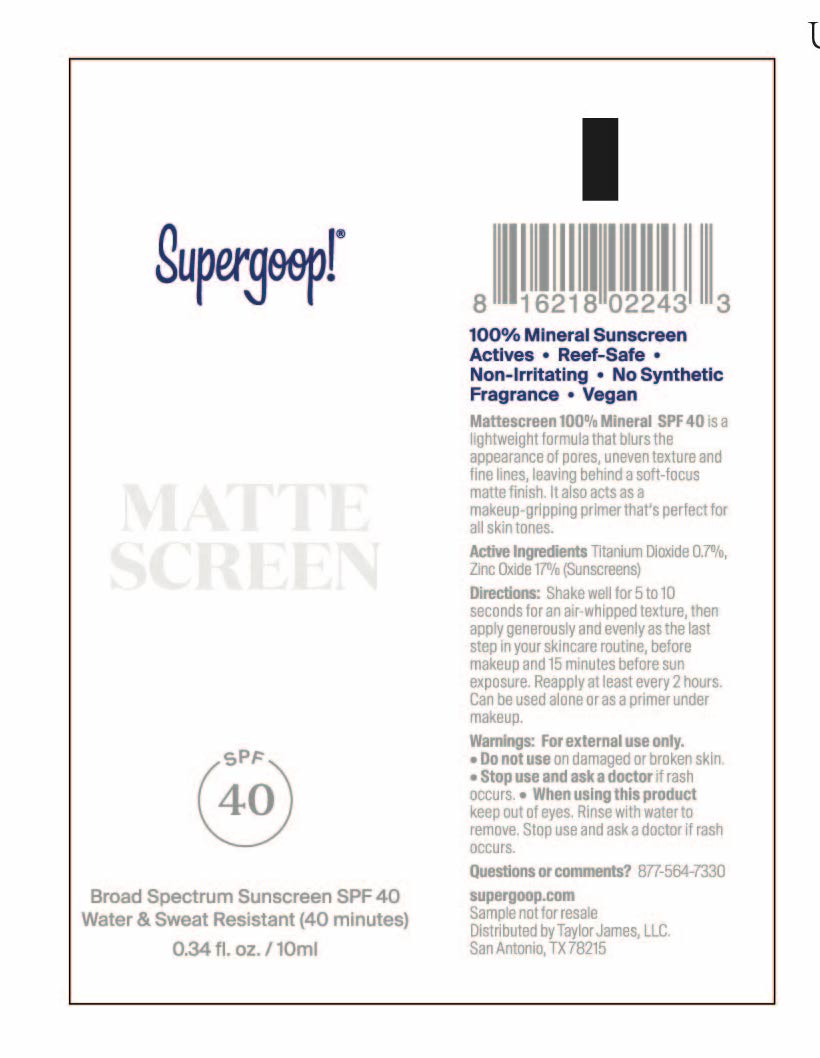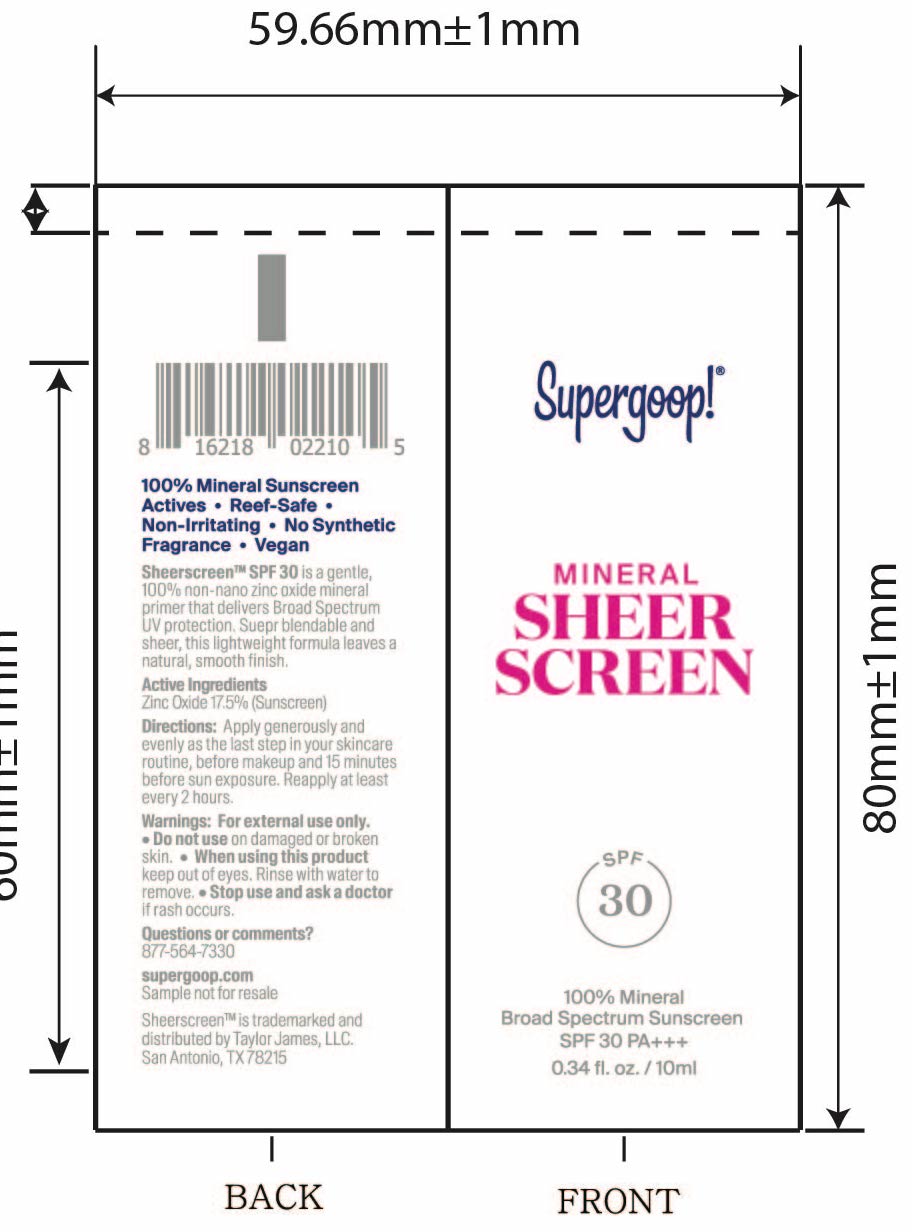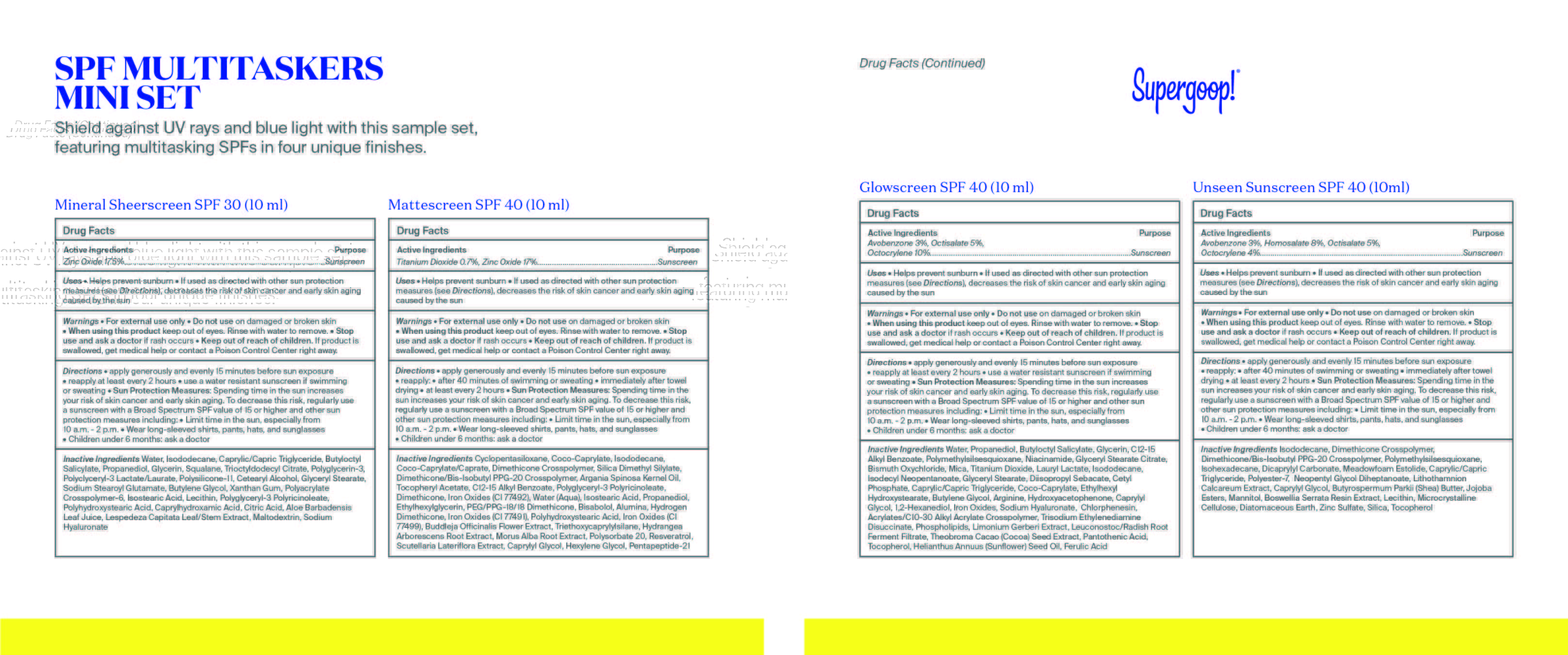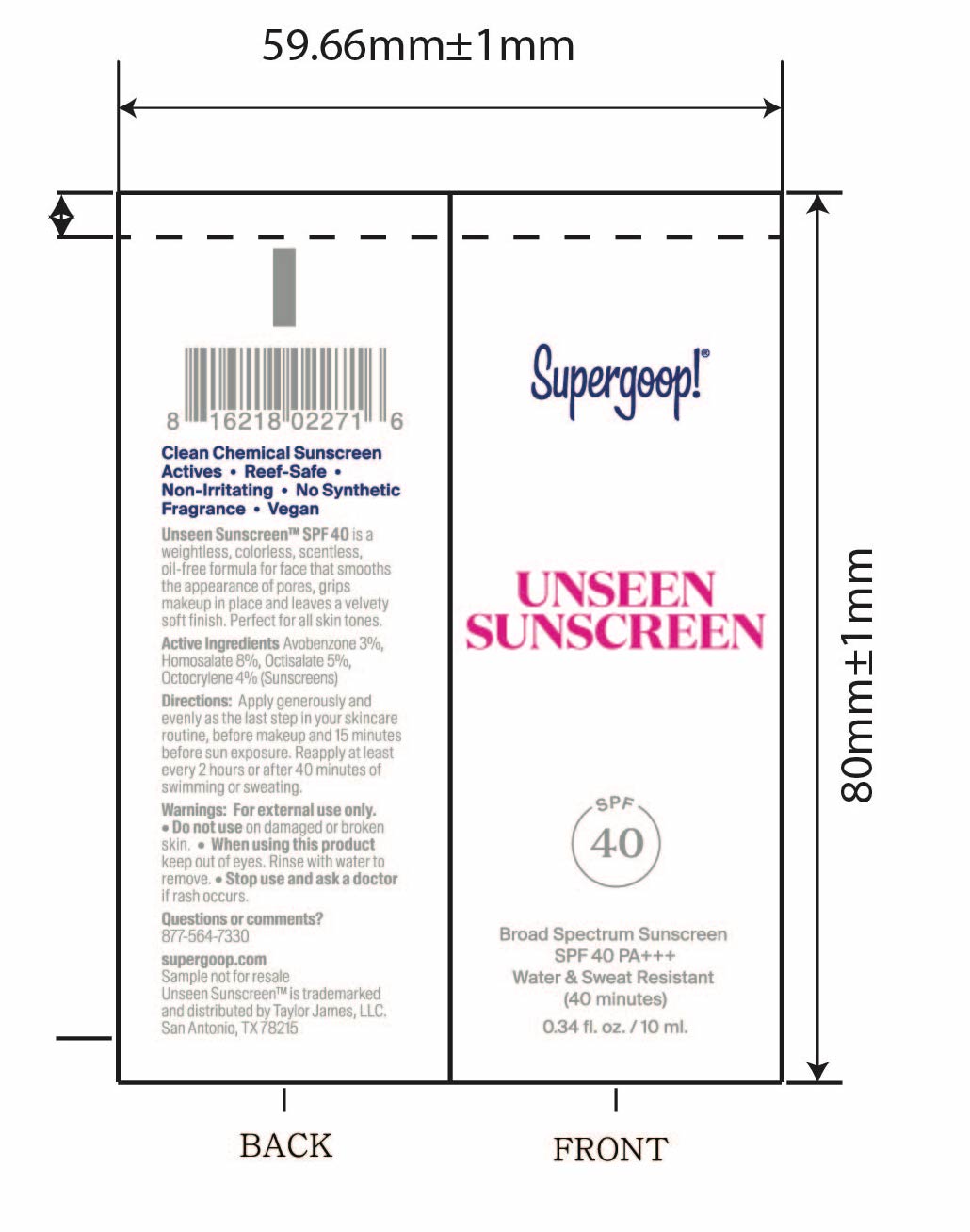 DRUG LABEL: SPF Multitaskers Mini Set
NDC: 82384-0015 | Form: KIT | Route: TOPICAL
Manufacturer: System Beauty, LLC
Category: otc | Type: HUMAN OTC DRUG LABEL
Date: 20211209

ACTIVE INGREDIENTS: OCTISALATE 5 g/100 mL; HOMOSALATE 8 g/100 mL; OCTOCRYLENE 4 g/100 mL; AVOBENZONE 3 g/100 mL; ZINC OXIDE 17.5 g/100 mL; TITANIUM DIOXIDE 0.7 g/100 mL; ZINC OXIDE 17 g/100 mL; OCTISALATE 5 g/100 mL; AVOBENZONE 3 g/100 mL; OCTOCRYLENE 10 g/100 mL
INACTIVE INGREDIENTS: DICAPRYLYL CARBONATE; MICROCRYSTALLINE CELLULOSE; POLYMETHYLSILSESQUIOXANE (4.5 MICRONS); SILICON DIOXIDE; ISODODECANE; DIATOMACEOUS EARTH; ZINC SULFATE; DIMETHICONE CROSSPOLYMER (450000 MPA.S AT 12% IN CYCLOPENTASILOXANE); LECITHIN, SOYBEAN; INDIAN FRANKINCENSE; PHYMATOLITHON CALCAREUM; CAPRYLYL GLYCOL; SHEA BUTTER; MANNITOL; POLYESTER-7; MEDIUM-CHAIN TRIGLYCERIDES; NEOPENTYL GLYCOL DIHEPTANOATE; DIMETHICONE/BIS-ISOBUTYL PPG-20 CROSSPOLYMER; ISOHEXADECANE; TOCOPHEROL; BUTYLOCTYL SALICYLATE; XANTHAN GUM; MALTODEXTRIN; GLYCERYL MONOSTEARATE; CITRIC ACID MONOHYDRATE; GLYCERIN; TRIOCTYLDODECYL CITRATE; POLYGLYCERYL-3 PENTARICINOLEATE; POLYHYDROXYSTEARIC ACID (2300 MW); CAPRYLHYDROXAMIC ACID; MEDIUM-CHAIN TRIGLYCERIDES; AMMONIUM ACRYLOYLDIMETHYLTAURATE, DIMETHYLACRYLAMIDE, LAURYL METHACRYLATE AND LAURETH-4 METHACRYLATE COPOLYMER, TRIMETHYLOLPROPANE TRIACRYLATE CROSSLINKED (45000 MPA.S); ISODODECANE; SODIUM STEAROYL GLUTAMATE; CETOSTEARYL ALCOHOL; ALOE VERA LEAF; LESPEDEZA CAPITATA FLOWERING TOP; HYALURONATE SODIUM; DIMETHICONE/VINYL DIMETHICONE CROSSPOLYMER (SOFT PARTICLE); BUTYLENE GLYCOL; PROPANEDIOL; SQUALANE; POLYGLYCERIN-3; ISOSTEARIC ACID; LECITHIN, SOYBEAN; WATER; LEVOMENOL; DIMETHICONE CROSSPOLYMER (450000 MPA.S AT 12% IN CYCLOPENTASILOXANE); FERRIC OXIDE RED; COCO-CAPRYLATE; SCUTELLARIA LATERIFLORA WHOLE; RESVERATROL; HEXYLENE GLYCOL; SILICA DIMETHYL SILYLATE; DIMETHICONE; ISOSTEARIC ACID; DIMETHICONE/BIS-ISOBUTYL PPG-20 CROSSPOLYMER; CYCLOMETHICONE 5; ISODODECANE; COCO-CAPRYLATE/CAPRATE; ARGAN OIL; .ALPHA.-TOCOPHEROL ACETATE; ALKYL (C12-15) BENZOATE; FERRIC OXIDE YELLOW; WATER; PROPANEDIOL; ETHYLHEXYLGLYCERIN; PEG/PPG-18/18 DIMETHICONE; ALUMINUM OXIDE; HYDROGEN DIMETHICONE (13 CST); POLYHYDROXYSTEARIC ACID (2300 MW); FERROSOFERRIC OXIDE; BUDDLEJA OFFICINALIS FLOWER; TRIETHOXYCAPRYLYLSILANE; HYDRANGEA ARBORESCENS ROOT; MORUS ALBA ROOT; POLYSORBATE 20; CAPRYLYL GLYCOL; 1,2-HEXANEDIOL; FERRIC OXIDE RED; COCOA; ALKYL (C12-15) BENZOATE; GLYCERYL MONOSTEARATE; CETYL PHOSPHATE; CHLORPHENESIN; GLYCERIN; PROPANEDIOL; BISMUTH OXYCHLORIDE; ISODECYL NEOPENTANOATE; DIISOPROPYL SEBACATE; HYALURONATE SODIUM; POLYMETHYLSILSESQUIOXANE (4.5 MICRONS); NIACINAMIDE; MICA; LAURYL LACTATE; LEUCONOSTOC/RADISH ROOT FERMENT FILTRATE; SUNFLOWER OIL; FERULIC ACID; MEDIUM-CHAIN TRIGLYCERIDES; CARBOMER INTERPOLYMER TYPE A (ALLYL SUCROSE CROSSLINKED); ISODODECANE; ETHYLHEXYL HYDROXYSTEARATE; TRISODIUM ETHYLENEDIAMINE DISUCCINATE; LIMONIUM GERBERI WHOLE; PANTOTHENIC ACID; TOCOPHEROL; TITANIUM DIOXIDE; GLYCERYL STEARATE CITRATE; WATER; BUTYLOCTYL SALICYLATE; COCO-CAPRYLATE; CAPRYLYL GLYCOL; BUTYLENE GLYCOL; ARGININE; HYDROXYACETOPHENONE

SPF Multitaskers Mini Set

Unseen Sunscreen SPF 40 active ingredients

Active Ingredients Purpose

Avobenzone 3% Sunscreen

Homosalate 8% Sunscreen

Octocrylene 4% Sunscreen

Octisalate 5% Sunscreen

Mineral Sheerscreen SPF 30 Active ingredients

Active Ingredient Purpose

Zinc Oxide 17.5% Sunscreen

Mineral Mattescreen SPF 40 Active ingredients

ACTIVE INGREDIENT PURPOSE

Active ingredients Purpose

Zinc oxide 17% Sunscreen

Titanium dioxide 0.7% Sunscreen

Glowscreen SPF 40 Active ingredients

Active Ingredients Purpose
Avobenzone 3% Sunscreen
Octisalate 5% Sunscreen
Octocylene 10% Sunscreen

Uses

Helps Prevent Sunburn

If used as directed with other sun protection measures (see Directions), decreases the risk of Skin cancer and early skin aging caused by the sun

Keep out of reach of children. If swallowed, get medical help or contact a Poison Control Center right away

Stop use and ask a doctor if rash occurs

Warnings

For External use only

Do not use on damaged or broken skin

When using this product, Keep out of eyes. Rinse with water to remove

Directions

- Apply generously and evenly 15 minutes before sun exposure
- Reapply:after 40 minutes of swimming or sweating

immediately after towel drying
at least every 2 hours

- Sun Protection Measures. Spending time in the sun increases your risk of skin

cancer and early skin aging. To decrease this risk, regularly use a sunscreen
with broad spectrum SPF of 15 or higher and other sun protection measures
including:

- limit time in the sun, especially from 10 a.m. - 2 p.m.
- Wear Long-sleeved shirts, pants, hats, and sunglasses
- Children under 6 months: Ask a doctor

Unseen Sunscreen SPF 40 Inactive Ingredients

Inactive Ingredients

Isododecane, Dimethicone Crosspolymer, Dimethicone/Bis-Isobutyl PPG-20 Crosspolymer, Polymethylsilsesquioxane, Isohexadecane, Dicrapylyl Carbonate, Meadowfoam Estolide, Caprylic/Capric Triglyceride, Polyester-7, Neopentyl Glycol Diheptanoate, Lithothamnion Calcareum Extract,Butyrospermum Parkii (Shea) Butter, Jojoba Esters, Mannitol, Boswellia Serrata Resin Extract, Lecithin, Microcrystalline Cellulose, Diatomaceous Earth, Zinc Sulfate, Silica, Tocopherol

Mineral Sheerscreen SPF 40 Inactive Ingredients

Inactive Ingredients

Alcohol Denat., Bisabolol, Brassica Campestris/Aleurites Fordi Oil Copolymer, Butyloctyl Salicylate, Caprylic/Capric Triglyceride, Capryloyl Glycerin/Sebacic Acid Copolymer, Dicaprylyl Carbonate, Diethylhexyl Syringylidenemalonate, Diheptyl Succinate, Diisooctyl Succinate, Ethyl Ferulate, Isododecane, Lauroyl Lysine, Mentha Piperita (Peppermint) Oil, Mentha Viridis (Spearmint) Leaf Oil, Nylon-12, PVP, Rosmarinus Officinalis (Rosemary) Leaf Oil, Silica Silylate

Mattescreen SPF 40 Inactive ingredients

Inactive ingredients

Cyclopentasiloxane, Coco-Caprylate, Isododecane, Coco-Caprylate/Caprate, Dimethicone Crosspolymer, Silica Dimethyl Silylate, Dimethicone/Bis-Isobutyl PPG-20 Crosspolymer, Argania Spinosa Kernel Oil, Cyclohexasiloxane, Tocopheryl Acetate, C12-15 Alkyl Benzoate, Polyglyceryl-3 Polyricinoleate, Dimethicone, Iron Oxides (CI 77492), Water (Aqua), Isostearic Acid, Cyclotetrasiloxane, Propanediol, Ethylhexylglycerin, PEG/PPG-18/18 Dimethicone, Bisabolol, Alumina, Hydrogen Dimethicone, Iron Oxides (CI 77491), Polyhydroxystearic Acid, Iron Oxides (CI 77499), Buddleja Officinalis Flower Extract, Triethoxycaprylylsilance, Tocopherol, Phenoxyethanol, Potassium Sorbate, Hydrangea Aborescens Root Extract, Morus Alba Root Extract, Polysorbate 20, Resveratrol, Scutellaria Lateriflora Extract, Caprylyl Glycol, Hexylene Glycol, Pentapeptide-21

Glow screen SPF 40 Inactive ingredients

Inactive Ingredients
Water, Propanediol, Butyloctyl Salicylate, Glycerin, C12-15 Alkyl Benzoate, Polymethylsilsesquioxane, Niacinamide, Glyceryl Stearate Citrate, Bismuth Oxychloride, Mica, Titanium Dioxide, Lauryl Lactate, Isododecane, Isodecyl Neopentanoate, Glyceryl Stearate, Diisopropyl Sebacate, Cetyl Phosphate, Caprylic/Capric Triglyceride, Coco-Caprylate, Ethylhexyl Hydroxystearate, Butylene Glycol, Arginine, Hydroxyacetophenone, Caprylyl Glycol, 1,2-Hexanediol, Iron Oxides, Sodium Hyaluronate, Chlorphenesin, Acrylates/C10-30 Alkyl Acrylate Crosspolymer, Trisodium Ethylenediamine Disuccinate, Phospholipids, Limonium Gerberi Extract, Leuconostoc/Radish Root Ferment Filtrate, Theobroma Cacao (Cocoa) Seed Extract, Pantothenic Acid, Tocopherol, Helianthus Annuus (sunflower) Seed Oil, Ferulic Acid

SPF Multitaskers Mini Set

Shield against UV rays and blue light with this sample set, featuring multitasking SPFs in four unique.

Mineral Sheerscreen SPF 30 (10 ml)

Mattescreen SPF 40 (10 ml)

Glowscreen SPF 40 (10 ml)

Unseen Sunscreen SPF 40 (10 ml)

Mineral Sheer Screen SPF 30

Mineral Sheer Screen

SPF 30

100% Mineral

Broad Spectrum Sunscreen SPF 30 PA+++

0.34 fl. oz./ 10 ml

Mattescreen SPF 40

Mattescreen SPF40

Broad Spectrum SPF 40

Water & Sweat Resistant (40 minutes)

0.34 fl oz. / 10ml

Glowscreen SPF 40

Broad Spectrum Sunscreen

SPF 40 PA+++

0.34 fl. oz. / 10 ml

Unseen Sunscreen SPF 40

Broad Spectrum Sunscreen SPF 40 PA +++

Water & Swear Resistant (40 minutes)

0.34 fl. oz. / 10 ml